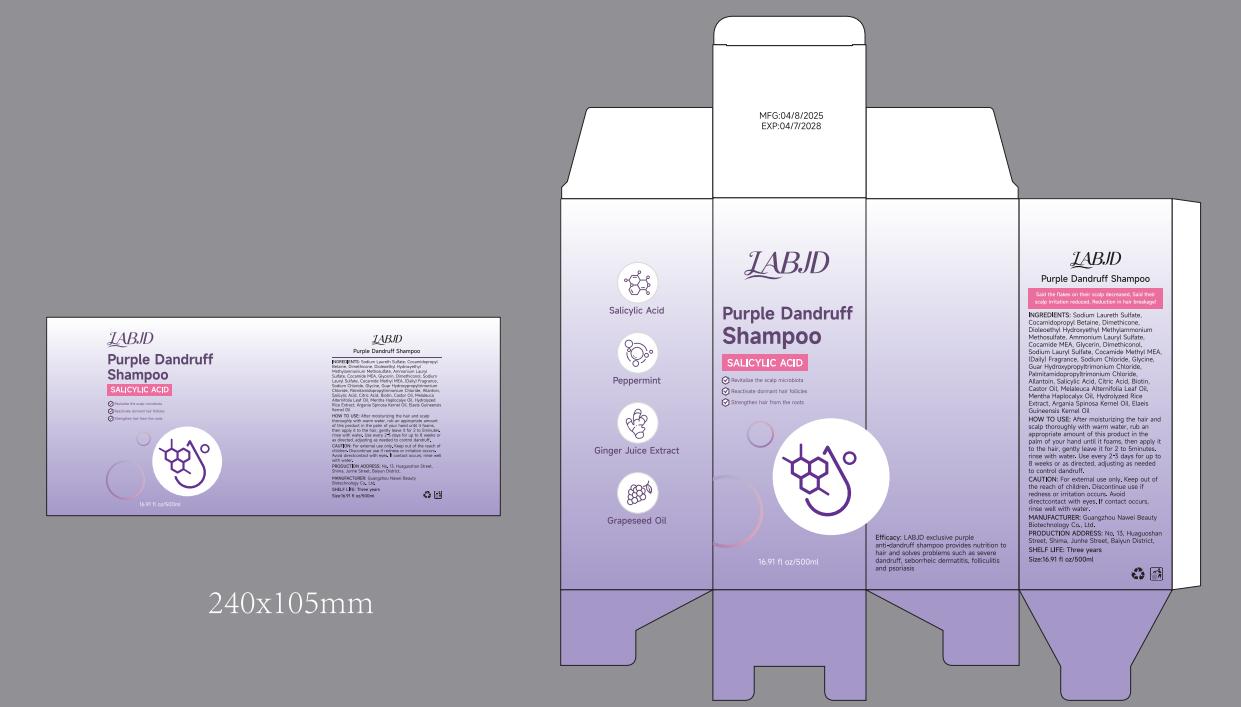 DRUG LABEL: Purple Dandruff
NDC: 85605-123 | Form: SHAMPOO
Manufacturer: Guangzhou Nawei Beauty Biotechnology Co., Ltd
Category: homeopathic | Type: HUMAN OTC DRUG LABEL
Date: 20250429

ACTIVE INGREDIENTS: COCAMIDE MEA 16 g/500 1
INACTIVE INGREDIENTS: SODIUM LAURETH SULFATE; DIMETHICONOL (70 CST); ELAEIS GUINEENSIS (PALM) KERNEL OIL; AMMONIUM LAURYL SULFATE; ARGANIA SPINOSA KERNEL OIL; GUAR HYDROXYPROPYLTRIMONIUM CHLORIDE; CITRIC ACID; BIOTIN; GLYCERIN; CASTOR OIL; MELALEUCA ALTERNIFOLIA (TEA TREE) LEAF OIL; DIOLEOYLETHYL HYDROXYETHYLMONIUM METHOSULFATE; SODIUM LAURYL SULFATE; ALLANTOIN; COCAMIDOPROPYL BETAINE; COCAMIDE METHYL MEA; SODIUM CHLORIDE; FRAGRANCE 13576; DIMETHICONE 1000; PALMITAMIDOPROPYLTRIMONIUM CHLORIDE

ACTIVE INGREDIENT

SODIUM LAURETH SULFATE

Keep out of the reach of children

INDICATIONS AND USAGE

After moisturizing the hair and scalp thoroughly with warm water,rub an appropriate amount of this product in the palm of your hand until it foams,then apply it to the hair,gently leave it for 2 to 5 minutes.

WARNINGS

CAUTION:For external use only.

DOSAGE AND ADMINISTRATION

Size:16.91 fl oz/500ml

INACTIVE INGREDIENT

COCAMIDOPROPYL BETAINE,DIMETHICONE,DIOLEOYLETHYL HYDROXYETHYLMONIUM METHOSULFATE,
AMMONIUM LAURYL SULFATE,COCAMIDE MEA,
GLYCERIN,DIMETHICONOL,SODIUM LAURYL SULFATE,COCAMIDE METHYL MEA,FRAGRANCE,SODIUM CHLORIDE,
GLYCINE,GUAR HYDROXYPROPYLTRIMONIUM CHLORIDE,PALMITAMIDOPROPYLTRIMONIUM CHLORIDE,ALLANTOIN
SALICYLIC ACID,CITRIC ACID,BIOTIN,CASTOR OIL,MELALEUCA ALTERNIFOLIA(TEATREE)LEAF OIL,
MENTHA HAPLOCALYX OIL,HYDROLYZED RICE EXTRACT,ARGANIA SPINOSA KERNEL OIL,

ELAEIS GUINEENSIS(PALM)KERNEL OIL

PURPOSE

purple anti-dandruff shampoo provides nutrition to hair and solves problems such as severe dandruff,seborrheic dermatitis,folliculitis and psoriasis